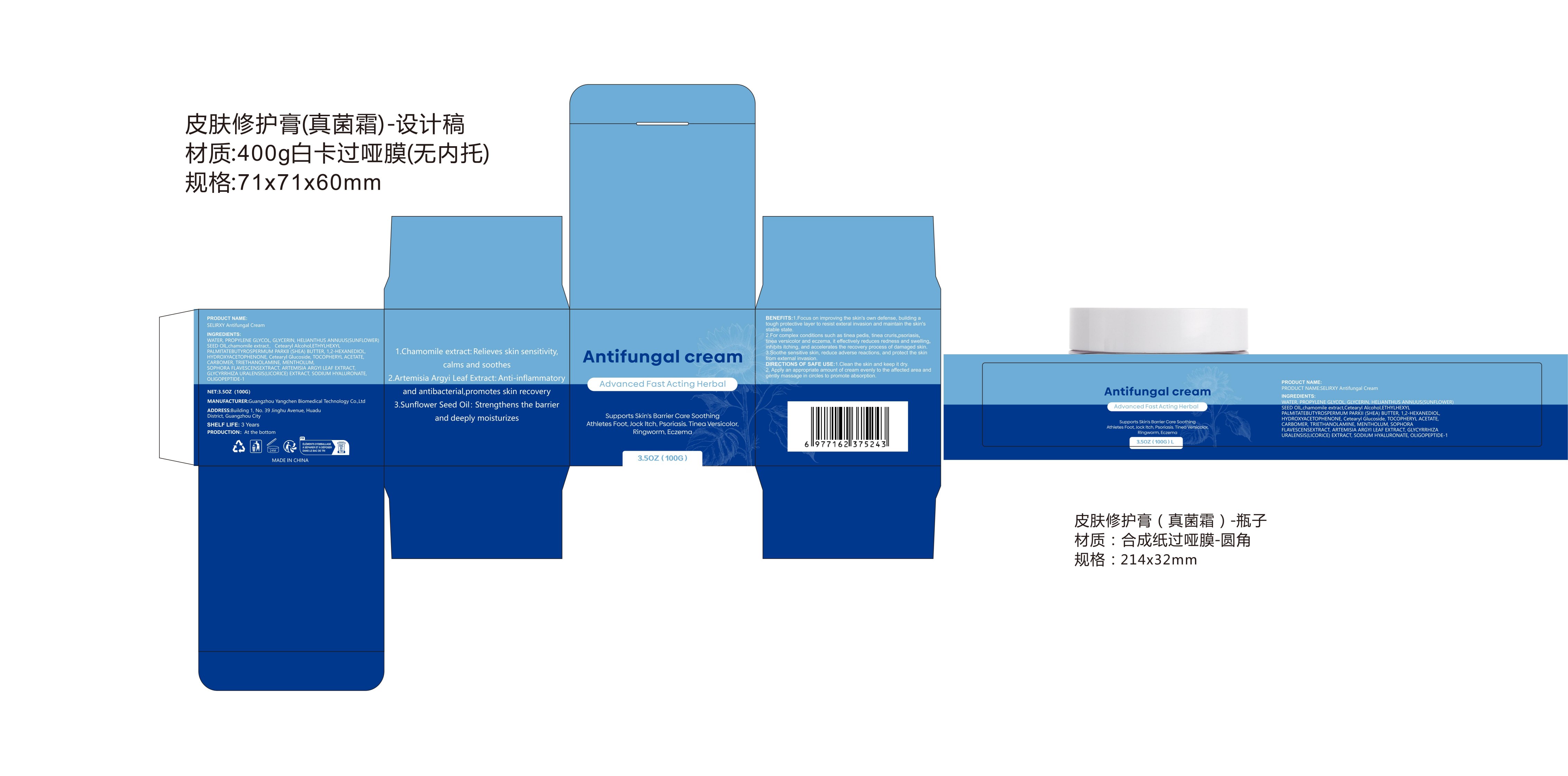 DRUG LABEL: Antifungal cream
NDC: 87123-003 | Form: CREAM
Manufacturer: Guangzhou Guoyoumi Biotechnology Co Ltd
Category: otc | Type: HUMAN OTC DRUG LABEL
Date: 20251115

ACTIVE INGREDIENTS: GLYCERIN 10 g/100 g
INACTIVE INGREDIENTS: AQUA

Active ingredients

GLYCERIN 10g

Purpose

Antifungal (for the treatment of fungal skin infections)

Uses[INDICATIONS & USAGE SECTION]

For the treatment of superficial fungal infections of the skin such as athlete's foot (tinea pedis), jock itch (tinea cruris), and ringworm (tinea corporis), caused by susceptible fung

Warnings

1. For external use only.2. Avoid contact with eyes, nose, mouth, and other mucous membranes. If contact occurs, rinse thoroughly with water.3. Do not use on broken or irritated skin.4. If irritation, redness, swelling, or itching worsens, discontinue use and consult a doctor.5. If condition persists after 4 weeks of use, consult a doctor.6. Do not use if you are allergic to any ingredient in this product.7. Keep out of reach of children. In case of accidental ingestion, get medical help or contact a Poison Control Center immediately.

Dosage and administration

Clean and dry the affected area thoroughly. Apply a thin layer of the cream to the affected skin and surrounding area twice daily (morning and evening) or as directed by a doctor. Continue use for 1-2 weeks after symptoms disappear to prevent recurrence.

- Do not use on children under 2 years of age unless directed by a doctor.- Do not use for vaginal yeast infections or nail fungal infections.- Do not use if the product is expired or the packaging is damaged.

When using section

1. Use only as directed.2. Do not cover the treated area with bandages or dressings unless directed by a doctor.3. Avoid using other topical products on the same area unless advised by a doctor.4. If using for athlete's foot, wear well-fitting, ventilated shoes and change socks daily.5. For jock itch, wear loose-fitting, breathable clothing.

stop use

Stop use and ask a doctor if:- Irritation, burning, stinging, or redness occurs and persists.- The infection spreads or worsens.- New symptoms appear.- Condition does not improve after 4 weeks of treatment.

Keep out of reach of children. If swallowed, get medical help or contact a Poison Control Center right away.

Inactive ingredients

WATER, PROPYLENE GLYCOL, HELIANTHUS ANNUUS(SUNFLOWER)SEED OlL,chamomile extract,Cetearyl Alcohol,ETHYLHEXYLPALMITATEBUTYROSPERMUM PARKII (SHEA) BUTTER, 1,2-HEXANEDIOLHYDROXYACETOPHENONE, Cetearyl Glucoside, TOCOPHERYL ACETATECARBOMER, TRIETHANOLAMINE, MENTHOLUM, SOPHORAFLAVESCENSEXTRACT, ARTEMISIA ARGYI LEAF EXTRACT, GLYCYRRHIZAURALENSIS(LICORICE) EXTRACT, SODIUM HYALURONATE, OLIGOPEPTIDE-1